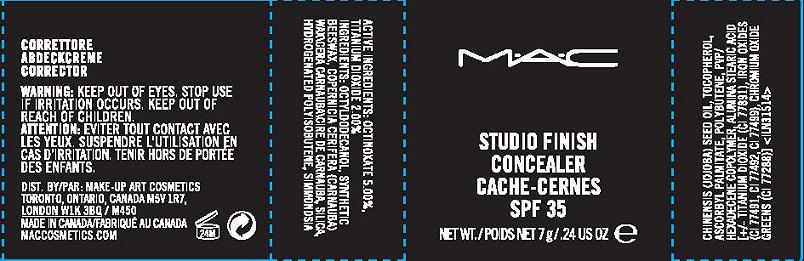 DRUG LABEL: STUDIO FINISH CONCEALER
NDC: 40046-0048 | Form: PASTE
Manufacturer: MAKEUP ART COSMETICS
Category: otc | Type: HUMAN OTC DRUG LABEL
Date: 20110826

ACTIVE INGREDIENTS: OCTINOXATE 5.0 g/100 g; TITANIUM DIOXIDE 2.00 g/100 g
INACTIVE INGREDIENTS: OCTYLDODECANOL; YELLOW WAX; CARNAUBA WAX; SILICON DIOXIDE; HYDROGENATED POLYBUTENE (1300 MW); JOJOBA OIL; ALPHA-TOCOPHEROL; ASCORBYL PALMITATE; POLYBUTENE (1400 MW); ALUMINUM OXIDE; STEARIC ACID; FERRIC OXIDE RED; CHROMIC OXIDE

ACTIVE INGREDIENT

ACTIVE INGREDIENTS: OCTINOXATE 5.00% [] TITANIUM DIOXIDE 2.00%

INACTIVE INGREDIENT

INACTIVE INGREDIENTS: OCTYLDODECANOL [] SYNTHETIC BEESWAX [] COPERNICIA CERIFERA (CARNAUBA) WAX [] SILICA [] HYDROGENATED POLYISOBUTENE [] SIMMONDSIA CHINENSIS (JOJOBA) SEED OIL [] TOCOPHEROL [] ASCORBYL PALMITATE [] POLYBUTENE [] PVP/HEXADECENE COPOLYMER [] ALUMINA [] STEARIC ACID [] [+/-(MAY CONTAIN) TITANIUM DIOXIDE (CI 77891) [] IRON OXIDES (CI 77491, CI 77492, CI 77499) [] CHROMIUM OXIDE GREENS (CI 77288)]

WARNINGS

WARNING: KEEP OUT OF EYES. STOP USE IF IRRITATION OCCURS. KEEP OUT OF REACH OF CHILDREN.

PACKAGE LABEL

PRINCIPAL DISPLAY PANEL

MAC

STUDIO FINISH CONCEALER

SPF 35

NET WT. 7 g/ 0.24 oz

MAKE UP ART COSMETICS

TORONTO, ONTARIO, CANADA,M5V 1R7